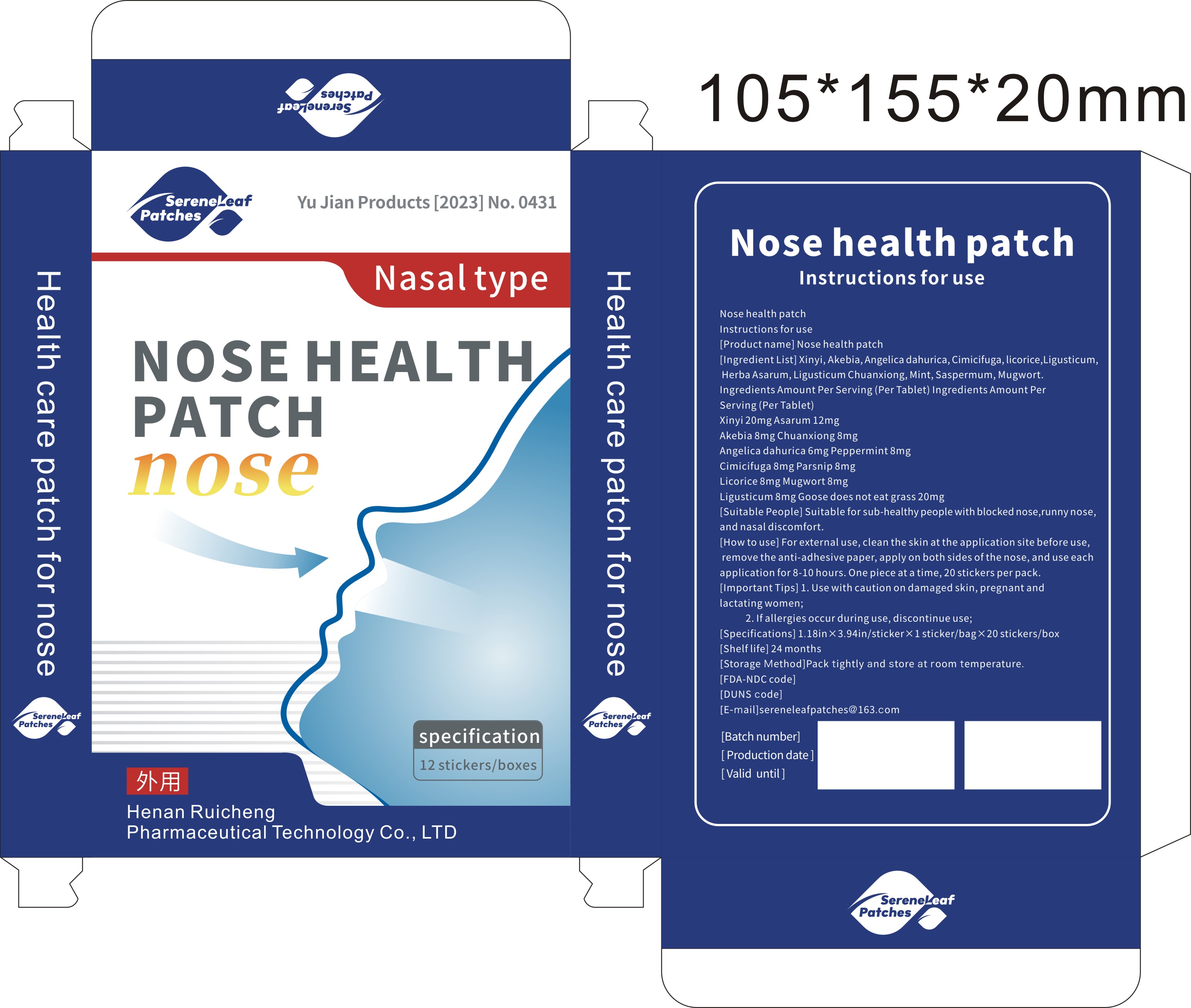 DRUG LABEL: Nasal health stickers
NDC: 84852-001 | Form: PATCH
Manufacturer: Jinhua Haimi Bird Trading Co., Ltd
Category: homeopathic | Type: HUMAN OTC DRUG LABEL
Date: 20241028

ACTIVE INGREDIENTS: BLACK COHOSH 0.05 g/1 1
INACTIVE INGREDIENTS: ASARUM ARIFOLIUM WHOLE; ANGELICA DAHURICA ROOT; HANSENIA FORBESII ROOT; CENTIPEDA MINIMA WHOLE; CONIOSELINUM ANTHRISCOIDES WHOLE; LIGUSTICUM WALLICHII ROOT; AKEBIA QUINATA STEM; MAGNOLIA ACUMINATA WHOLE; SAPOSHNIKOVIA DIVARICATA ROOT; LICORICE

Nasal health stickers

ACTIVE INGREDIENT

BLACK COHOSH 5%

PURPOSE

Suitable for sub-healthy people with blocked nose,runnynose,and nasaldiscomfort.

KEEP OUT OF REACH OF CHILDREN SECTION

INDICATIONS AND USAGE

Suitable for sub-healthy people with blocked nose,runnynose,and nasaldiscomfort.

WARNINGS

[lmportantTips]
For external use only
1.Use with caution on damaged skin, pregnant andlactatingwomen;
2. lfallergies occur during use, discontinue use,

DOSAGE AND ADMINISTRATION

[How to use] For external use, clean the skin at the application site before use,remove the anti-adhesive paper, applyon both sides ofthe nose, and use eachapplication for8-10 hours.One piece at a time, 20 stickers per pack.

INACTIVE INGREDIENT

ASARUM ARIFOLIUM WHOLE
ANGELICA DAHURICA ROOT
HANSENIA FORBESII ROOT
MAGNOLIA ACUMINATA WHOLE
SAPOSHNIKOVIA DIVARICATA ROOT
LICORICE
CENTIPEDA MINIMA WHOLE
CONIOSELINUM ANTHRISCOIDES WHOLE
LIGUSTICUM WALLICHII ROOT
AKEBIA QUINATA STEM